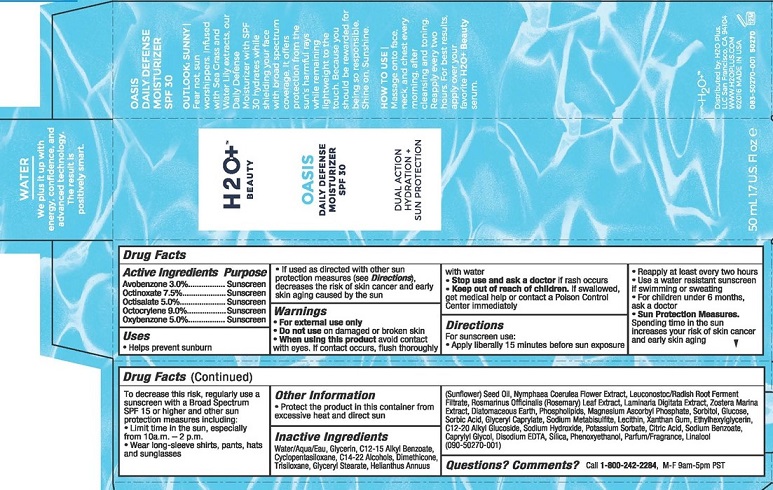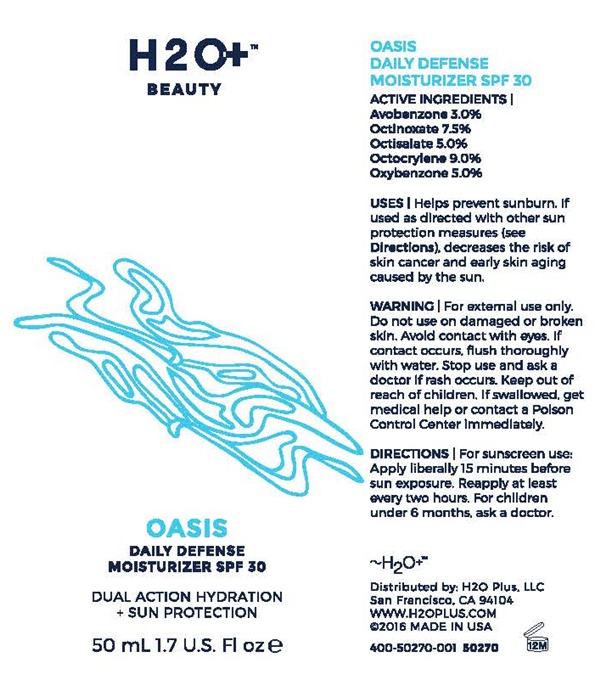 DRUG LABEL: Oasis Daily Defense
NDC: 54111-128 | Form: CREAM
Manufacturer: Bentley Laboratories, LLC
Category: otc | Type: HUMAN OTC DRUG LABEL
Date: 20181219

ACTIVE INGREDIENTS: AVOBENZONE 1.5 g/50 mL; OCTINOXATE 3.75 g/50 mL; OCTISALATE 2.5 g/50 mL; OCTOCRYLENE 4.5 g/50 mL; OXYBENZONE 2.5 g/50 mL
INACTIVE INGREDIENTS: WATER; GLYCERIN; ALKYL (C12-15) BENZOATE; CYCLOMETHICONE 5; C14-22 ALCOHOLS; DIMETHICONE; TRISILOXANE; GLYCERYL MONOSTEARATE; SUNFLOWER OIL; NYMPHAEA CAERULEA FLOWER; LEUCONOSTOC/RADISH ROOT FERMENT FILTRATE; ROSEMARY; LAMINARIA DIGITATA; ZOSTERA MARINA SEED; DIATOMACEOUS EARTH; LECITHIN, SOYBEAN; MAGNESIUM ASCORBYL PHOSPHATE; SORBITOL; DEXTROSE, UNSPECIFIED FORM; SORBIC ACID; GLYCERYL CAPRYLATE; SODIUM METABISULFITE; XANTHAN GUM; ETHYLHEXYLGLYCERIN; C12-20 ALKYL GLUCOSIDE; EDETATE DISODIUM; SILICON DIOXIDE; PHENOXYETHANOL; LINALOOL, (+/-)-

Oasis - 128

Drug Facts Active Ingredients

Avobenzone 3.0%

Octinoxare 7.5%

Octisalate 5.0%

Octocrylene 9.0%

Oxybenzone 5.0%

Purpose

Sunscreen

Keep out of reach of children

If swallowed, get medical help or contact a Poison Control Center immediately.

Uses

- Helps prevent sunburn

- If used as directed with other sun protection measures (see Directions), decreases the risk of skin cancer and early skin aging caused by the sun

Warnings

- For external use only

Do not use

on damaged or broken skin

When using this product

aoid contact with eyes. If contact occurs, flush thoroughly with water

Stop use and ask a doctor

if rash occurs

Directions

For sunscreen use:

- Apply liberally 15 minutes before sun exposure
- Rapply at least every two hours
- Use a water resistant sunscreen if swimming or sweating
- For children under 6 months, ask a doctor
- Sun Protection Measures.

Spending time in the sun increases your risk of skin cancer and early skin aging

To decrease this risk, regularly use a sunscreen with a Broad Spectrum SPF 15 or higher and other sun protection measures including:

- Limit time in the sun, especially from 10a.m. - 2 p.m.
- Wear long sleeve shirts, pants, hats and sunglasses

Other Information

- Protect the product in this container from excessive heat and direct sun

Inactive Ingredients

Water/Aqua/Eau, Glycerin, C12-15 Alkyl benzoate, Cyclopentasiloxane, C14-22 Alcohols, Dimethicone, Trisiloxane, Glyceryl Stearate, Helianthus Annuus (Sunflower) Seed Oil, Nymphaea Coerulea Flower Extract, Leuconostoc/Radish Root Ferment Filtrate, Rosmarinus Officinalis (Rosemary) Leaf Extract, Laminaria Digitata Extract, Zostera Marina Extract, Diatomaceous Earth, Phospholipids, Magnesium Ascorbyl Phosphate, Sorbitol, Glucose, Sorbic Acid, Glyceryl Caprylate, Sodium Metabisulfite, Lecithin, Xanthan Gum, Ethylhexylglycerin, C12-20 Alkyl Glucoside, Sodium Hydroxide, Potassium Sorbate, Citric Acid, Sodium Benzoate, caprylyl Glycol, Disodium EDTA, Silica, Phenoxyethanol, Parfum/Fragrance, Linalool (090-50270-001)

Questions? Comments?

Call 1-800-242-2284, M-F 9an - 5pm PST

Oasis product label

H2O+™

BEAUTY

OASIS
DAILY DEFENSE MOISTURIZER

SPF 30

DUAL ACTION HYDRATION + SUN PROTECTION

50mL 1.7 U.S. Fl oz

WATER

We plus it up with energy, confidence, and advanced technology. The result is positively smart.

OASIS
DAILY DEFENSE MOISTURIZER
SPF 30

OUTLOOKS SUNNY l

Fear not, sun worshippers. Infused with Sea Grass and Water Lily extracts, our Daily Defense Moisturizer with SPF 30 hydrates while shielding your face with broad spectrum coverage.It offers protection from the sun's harmful rays while remaining lightweight to the touch. Because you should be rewarded for being so responsible. Shine on. Sunshine.

HOW TO USE l

Massage onto face, neck, and chest every morning, after cleansing and toning. Reapply every two hours. For best resulths, apply over your favorite H2O+ Beauty serum.

H2O™

Distributed by: H20 Plus, LLC

San francisco, CA 94104

www.H2OPLUS.COM

2016 MADE IN USA

083-50270-001 50270